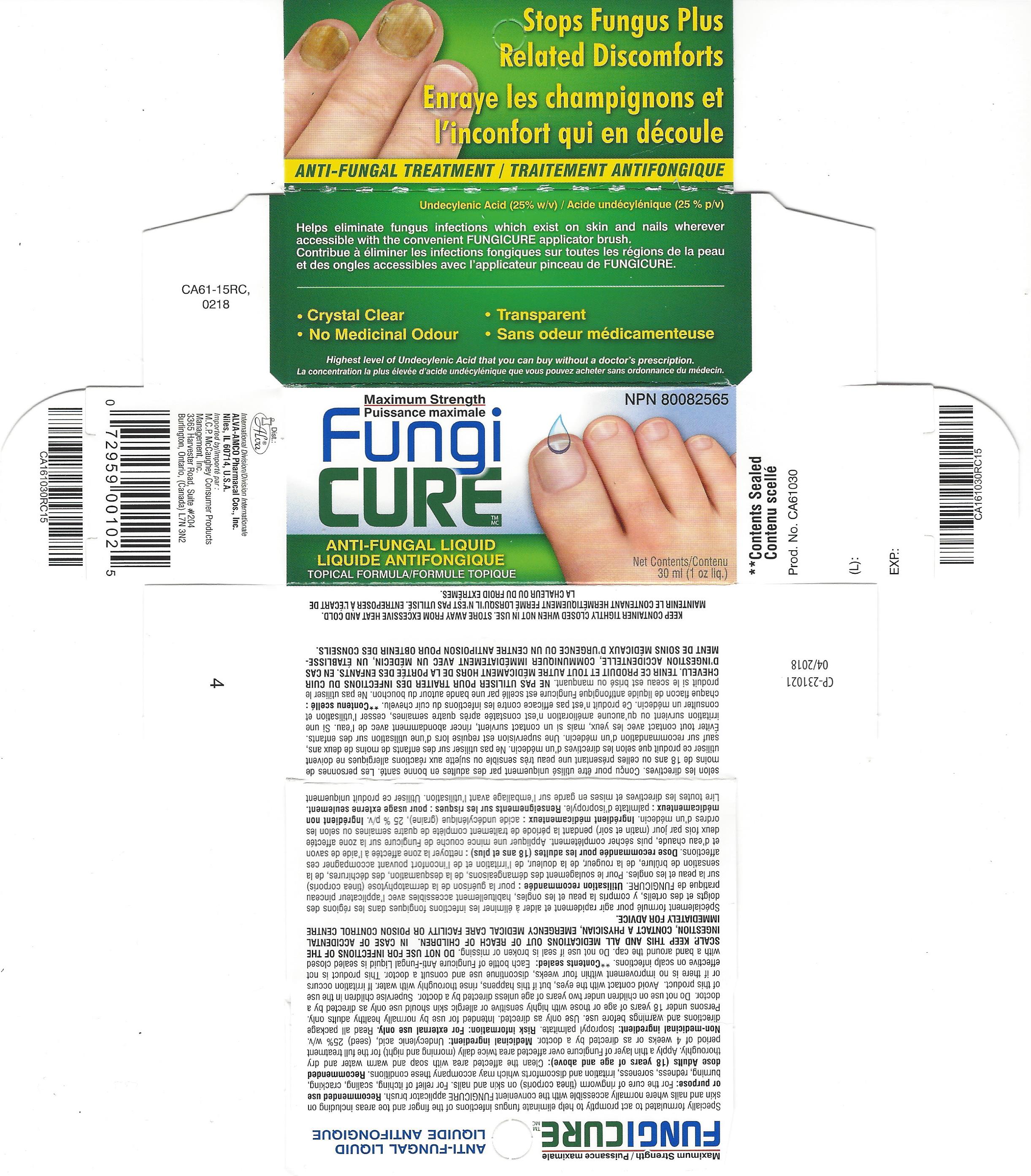 DRUG LABEL: Fungicure
NDC: 52389-198 | Form: LIQUID
Manufacturer: Kobayashi Healthcare International, Inc.
Category: otc | Type: HUMAN OTC DRUG LABEL
Date: 20251219

ACTIVE INGREDIENTS: UNDECYLENIC ACID 250 mg/1 mL
INACTIVE INGREDIENTS: ISOPROPYL PALMITATE

Maximum Strength Fungicure Liquid 25%